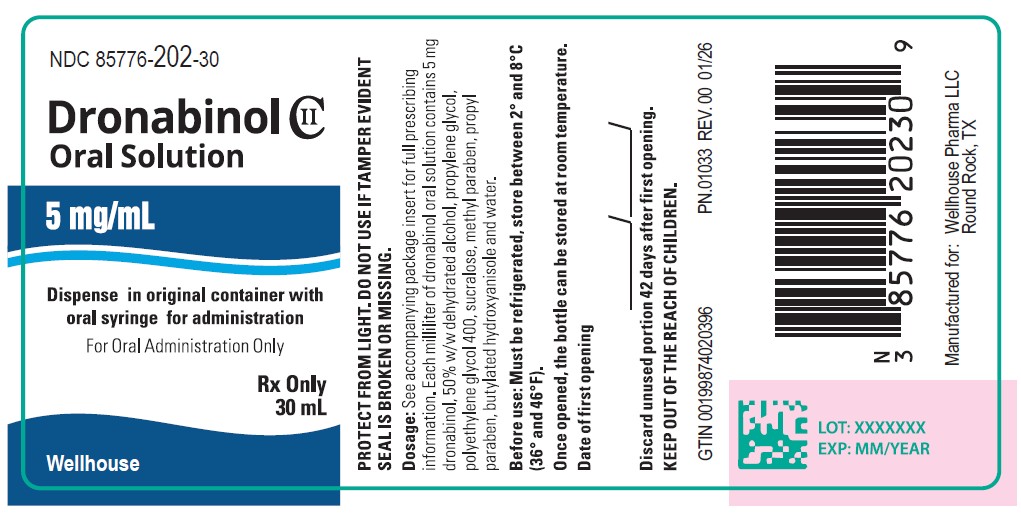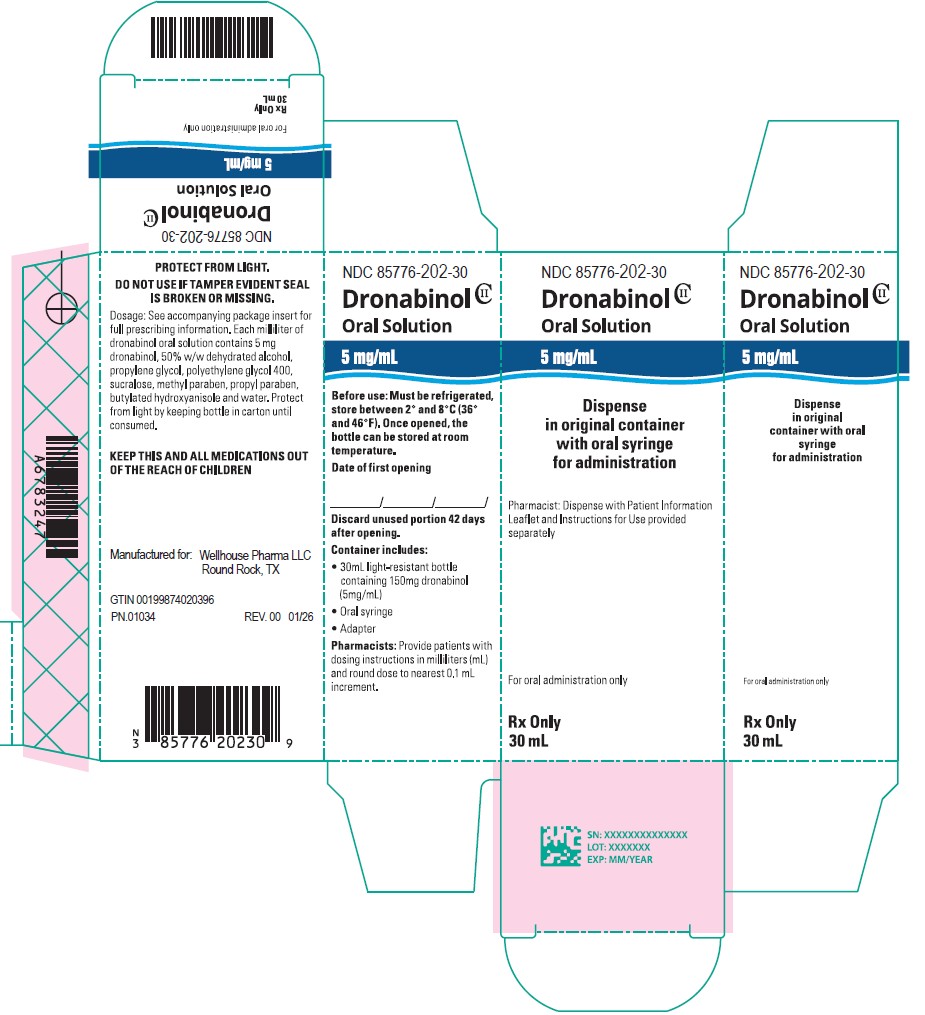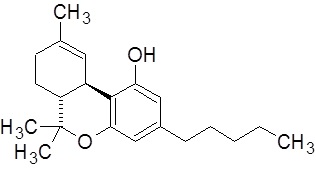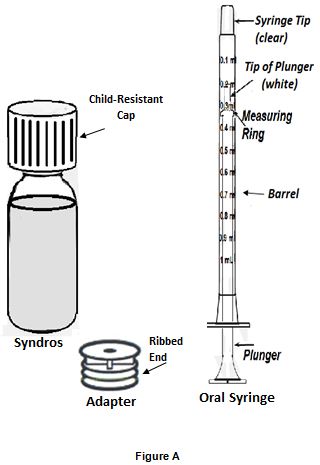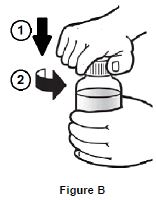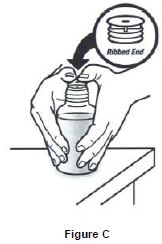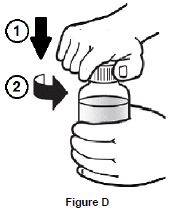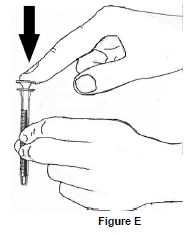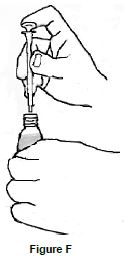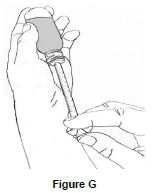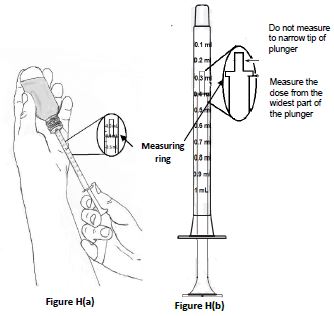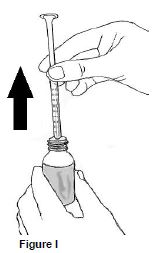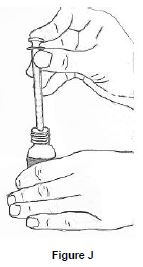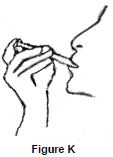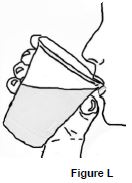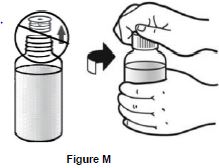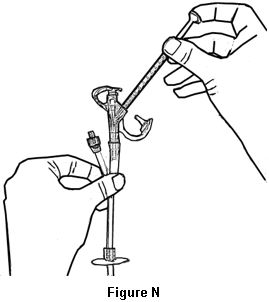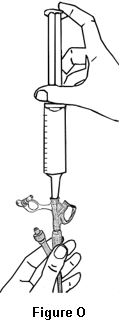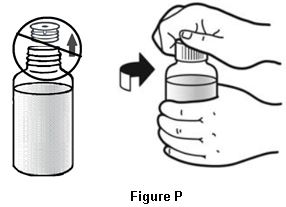 DRUG LABEL: DRONABINOL
NDC: 85776-202 | Form: SOLUTION
Manufacturer: Wellhouse Pharma, LLC
Category: prescription | Type: HUMAN PRESCRIPTION DRUG LABEL
Date: 20260211
DEA Schedule: CII

ACTIVE INGREDIENTS: DRONABINOL 5 mg/1 mL

HIGHLIGHTS OF PRESCRIBING INFORMATION

These highlights do not include all the information needed to use DRONABINOL ORAL SOLUTION safely and effectively. See full prescribing information for DRONABINOL ORAL SOLUTION.
DRONABINOL Oral Solution, CII
Initial U.S. Approval: 1985

1 INDICATIONS AND USAGE

Dronabinol oral solution is a cannabinoid indicated in adults for the treatment of:

- anorexia associated with weight loss in patients with AIDS. (1)
- nausea and vomiting associated with cancer chemotherapy in patients who have failed to respond adequately to conventional antiemetic treatments. (1)

2 DOSAGE AND ADMINISTRATION

Administration (2.1):

- Always use the enclosed calibrated oral dosing syringe.
- The calibrated oral syringe measures a maximum dronabinol oral solution dose of 5 mg. If the prescribed dose is greater than 5 mg, the total dose will need to be divided and drawn up in two or more portions using the oral syringe.
- Take dronabinol oral solution with a full glass of water (6 to 8 ounces).
- Dronabinol oral solution can be administered via silicone enteral feeding tubes.

Anorexia Associated with Weight Loss in Adult Patients with AIDS (2.2):

- The recommended starting dosage is 2.1 mg orally twice daily, one hour before lunch and dinner.
- See the full prescribing information for dosage titration to manage adverse reactions and to achieve desired therapeutic effect.

Nausea and Vomiting Associated with Chemotherapy in Adult Patients Who Failed Conventional Antiemetics (2.3):

- The recommended starting dosage is 4.2 mg/m ^2, administered 1 to 3 hours prior to chemotherapy, then every 2 to 4 hours after chemotherapy for a total of 4 to 6 doses per day. Administer the first dose on an empty stomach at least 30 minutes prior to eating; subsequent doses can be taken without regard to meals.
- See the full prescribing information for dosage titration to manage adverse reactions and to achieve desired therapeutic effect.

3 DOSAGE FORMS AND STRENGTHS

Oral Solution: 5 mg/ mL (3)

4 CONTRAINDICATIONS

- Sensitivity to dronabinol or alcohol. (4)
- History of hypersensitivity reaction to alcohol. (4)
- Patients receiving, or have received, disulfiram- or metronidazole-containing products within the past 14 days. (4, 5.3, 7.1)

5 WARNINGS AND PRECAUTIONS

- Neuropsychiatric Adverse Reactions: May cause psychiatric and cognitive effects and impair mental and/or physical abilities. Avoid use in patients with a psychiatric history. Monitor for symptoms and avoid concomitant use of drugs with similar effects. Inform patients not to operate motor vehicles or other dangerous machinery until they are reasonably certain that dronabinol oral solution does not affect them adversely. (5.1)
- Hemodynamic Instability: Patients with cardiac disorders may experience hypotension, hypertension, syncope, or tachycardia. Avoid concomitant use of drugs with similar effects and monitor for hemodynamic changes after initiating or increasing the dosage of dronabinol oral solution. (5.2)
- Interaction with Disulfiram and Metronidazole: May cause disulfiram-like reaction. Discontinue products containing disulfiram or metronidazole at least 14 days before and do not administer 7 days after treatment with dronabinol oral solution. (4, 5.3, 7.1)
- Seizures and Seizure-like Activity: Weigh the potential risk versus benefits before prescribing dronabinol oral solution to patients with a history of seizures, including those requiring anti-epileptic medication or with other factors that lower the seizure threshold. Monitor patients and discontinue if seizures occur. (5.4)
- Multiple Substance Abuse: Assess risk for abuse or misuse in patients with a history of substance abuse or dependence, prior to prescribing dronabinol oral solution and monitor for the development of associated behaviors or conditions. (5.5)
- Paradoxical Nausea, Vomiting, or Abdominal Pain: Consider reduction or discontinuation, if worsening of symptoms while on treatment. (5.6)
- Toxicities Related to Propylene Glycol in Preterm Neonates: The safety and effectiveness of dronabinol oral solution have not been established in pediatric patients. Avoid use in preterm neonates in the immediate postnatal period. (5.7)

6 ADVERSE REACTIONS

Most common adverse reactions (≥3%) are: abdominal pain, dizziness, euphoria, nausea, paranoid reaction, somnolence, thinking abnormal, and vomiting. (6.1)

To report SUSPECTED ADVERSE REACTIONS, contact Wellhouse Pharma, LLC at 1-844-558-8289 or FDA at MedWatch phone number 1-800-FDA-1088 or www.fda.gov/medwatch.

7 DRUG INTERACTIONS

- Inhibitors and Inducers of CYP2C9 and CYP3A4: May alter dronabinol systemic exposure; monitor for dronabinol-related adverse reactions or loss of efficacy. (7.2)
- Highly Protein-Bound Drugs: Potential for displacement of other drugs from plasma proteins; monitor for adverse reactions to concomitant narrow therapeutic index drugs (e.g., warfarin, cyclosporine, or amphotericin B) when initiating or increasing the dosage of dronabinol oral solution. (7.3)

8 USE IN SPECIFIC POPULATIONS

- Pregnancy: May cause fetal harm. (8.1)
- Lactation: Advise HIV infected women not to breastfeed due to the potential for HIV transmission. (8.2)
- Geriatric Use: Elderly patients may be more sensitive to the neuropsychiatric and postural hypotensive effects. Consider a lower starting dose in elderly patients. (2.2, 2.3, 5.1, 5.2, 8.5)

FULL PRESCRIBING INFORMATION

1 INDICATIONS AND USAGE

Dronabinol oral solution is indicated in adults for the treatment of:

- anorexia associated with weight loss in patients with Acquired Immune Deficiency Syndrome (AIDS).
- nausea and vomiting associated with cancer chemotherapy in patients who have failed to respond adequately to conventional antiemetic treatments.

2 DOSAGE AND ADMINISTRATION

2.1 Important Administration Instructions

Oral Administration

- Always use the enclosed calibrated oral dosing syringe when administering dronabinol oral solution to ensure the dose is measured and administered accurately.
- The calibrated oral syringe measures a maximum dronabinol oral solution dose of 5 mg. If the prescribed dose is greater than 5 mg, the total dose will need to be divided and drawn up in two or more portions using the oral syringe.
- Take each dose of dronabinol oral solution with a full glass of water (6 to 8 ounces).
- For information on dosing dronabinol with regard to meals, see Dosage and Administration 2.2 and 2.3.

Administration via Feeding Tube (silicone only, greater than or equal to 14 French)

Dronabinol oral solution can be administered via enteral feeding tubes that are manufactured using silicone, size greater than or equal to 14 French, such as Naso-Gastric (NG), Gastrostomy Tube (G-tube), Percutaneous Endoscopic Gastrostomy tube (PEG-tube) and Gastro-Jejunostomy tube (GJ-tube). Do not use tubes manufactured of polyurethane.

1. Draw up the prescribed dose with the calibrated dosing syringe packaged with dronabinol oral solution.
2. If the prescribed dose is greater than 5 mg, the total dose will need to be divided and drawn up in two or more portions using the oral syringe.
3. Using the calibrated dosing syringe, administer the dose via the feeding tube.
4. Using a catheter-tip syringe, flush the feeding tube with 30 mL of water.

2.2 Anorexia Associated with Weight Loss in Adult Patients with AIDS

Starting Dosage

The recommended adult starting dosage of dronabinol oral solution is 2.1 mg orally twice daily, one hour before lunch and one hour before dinner.

In elderly patients, or patients unable to tolerate 2.1 mg twice daily, consider initiating dronabinol oral solution at 2.1 mg once daily one hour before dinner or at bedtime to reduce the risk of central nervous system (CNS) symptoms [see Use in Specific Populations (8.5)].

Dosing later in the day may reduce the frequency of Central Nervous System (CNS) adverse reactions. CNS adverse reactions are dose-related [see Warnings and Precautions (5.1)]; therefore, monitor patients and reduce the dosage as needed. If CNS adverse reactions of feeling high, dizziness, confusion, and somnolence occur, they usually resolve in 1 to 3 days and usually do not require dosage reduction. If CNS adverse reactions are severe or persistent, reduce the dosage to 2.1 mg once daily one hour before dinner or in the evening at bedtime.

Dosage Titration

- If tolerated and further therapeutic effect is desired, the dosage may be increased gradually to 2.1 mg one hour before lunch and 4.2 mg one hour before dinner. Increase the dose of dronabinol oral solution gradually in order to reduce the frequency of dose-related adverse reactions [see Warnings and Precautions (5.1)].
- Most patients respond to 2.1 mg twice daily, but the dose may be further increased to 4.2 mg one hour before lunch and 4.2 mg one hour before dinner, as tolerated to achieve a therapeutic effect.
- Maximum Dosage: 8.4 mg twice daily.

2.3 Nausea and Vomiting Associated with Cancer Chemotherapy in Adult Patients Who Failed Conventional Antiemetics

Starting Dosage

The recommended starting dosage of dronabinol oral solution is 4.2 mg/m^2 orally administered 1 to 3 hours prior to chemotherapy and then every 2 to 4 hours after chemotherapy for a total of 4 to 6 doses per day.

- Calculate the starting dose by following the steps below:
  - Starting dose (mg) = Patient body surface area (BSA) in m ^2 multiplied by 4.2 mg/m ^2
  - Round dose to the nearest 0.1 mg increment
  - Convert from milligrams (mg) to milliliters (mL):
    - Starting dose (mg) rounded to the nearest 0.1 mg increment divided by 5 = Starting dose in milliliters (mL)
  - To correspond with the calibrated oral dosing syringe, the dose may need to be rounded to the nearest 0.1 mL increment.

In elderly patients, consider initiating dronabinol oral solution at 2.1 mg/m^2 once daily 1 to 3 hours prior to chemotherapy to reduce the risk of CNS symptoms [see Use in Specific Populations (8.5)].

Because food delays the absorption of dronabinol oral solution, administer the first dose on an empty stomach at least 30 minutes before eating. Subsequent doses can be taken without regard to meals.

Because food can substantially change the systemic exposure to dronabinol and its active metabolite, the timing of dosing in relation to meal times should be kept consistent for each chemotherapy cycle, once the dosage has been determined from the titration process.

Dosage Titration

- The dosage can be titrated to clinical response during a chemotherapy cycle or subsequent cycles, based upon initial effect, as tolerated to achieve a clinical effect, in increments of 2.1 mg/m^2.
- Maximum Dosage: 12.6 mg/m ^2 per dose for 4 to 6 doses per day.
- Adverse reactions are dose-related and psychiatric symptoms increase significantly at the maximum dosage [see Warnings and Precautions (5.1)].

Monitor patients for adverse reactions and consider decreasing the dose to 2.1 mg once daily 1 to 3 hours prior to chemotherapy to reduce the risk of CNS adverse reactions.

3 DOSAGE FORMS AND STRENGTHS

Oral Solution: 5 mg/mL, a clear, pale yellow to brown solution.

4 CONTRAINDICATIONS

Dronabinol oral solution is contraindicated in patients:

- with a history of a hypersensitivity reaction to dronabinol. Reported hypersensitivity reactions to dronabinol include lip swelling, hives, disseminated rash, oral lesions, skin burning, flushing, throat tightness [see Adverse Reactions (6.2)].
- with a history of a hypersensitivity reaction to alcohol.
- who are receiving, or have recently received, disulfiram- or metronidazole-containing products within 14 days [see Warning and Precautions (5.3)]. Dronabinol oral solution contains 50% (w/w) dehydrated alcohol and 5.5% (w/w) propylene glycol.

5 WARNINGS AND PRECAUTIONS

5.1 Neuropsychiatric Adverse Reactions

Psychiatric Adverse Reactions

Dronabinol has been reported to exacerbate mania, depression, or schizophrenia. Prior to initiating treatment with dronabinol oral solution, screen patients for a history of these illnesses. Avoid use in patients with a psychiatric history or, if the drug cannot be avoided, monitor patients for new or worsening psychiatric symptoms during treatment. Also, avoid concomitant use with other drugs that are associated with similar psychiatric effects.

Cognitive Adverse Reactions

Use of dronabinol oral solution has been associated with cognitive impairment and altered mental state. Reduce the dose of dronabinol oral solution or discontinue use of dronabinol oral solution if signs or symptoms of cognitive impairment develop. Elderly and pediatric patients may be more sensitive to the neurological and psychoactive effects of dronabinol oral solution [see Use in Specific Populations (8.4, 8.5)].

Hazardous Activities

Dronabinol oral solution can cause and may impair the mental and/or physical abilities required for the performance of hazardous tasks such as driving a motor vehicle or operating machinery. Concomitant use of other drugs that cause dizziness, confusion, sedation, or somnolence such as CNS depressants may increase this effect (e.g., barbiturates, benzodiazepines, lithium, opioids, buspirone, scopolamine, antihistamines, tricyclic antidepressants, other anticholinergic agents, and muscle relaxants). Inform patients not to operate motor vehicles or other dangerous machinery until they are reasonably certain that dronabinol oral solution does not affect them adversely.

5.2 Hemodynamic Instability

Patients may experience occasional hypotension, possible hypertension, syncope, or tachycardia while taking dronabinol oral solution [see Clinical Pharmacology (12.2)]. Patients with cardiac disorders may be at higher risk. Avoid concomitant use of other drugs that are also associated with similar cardiac effects (e.g., amphetamines, other sympathomimetic agents, atropine, amoxapine, scopolamine, antihistamines, other anticholinergic agents, amitriptyline, desipramine, other tricyclic antidepressants). Monitor patients for changes in blood pressure, heart rate, and syncope after initiating or increasing the dosage of dronabinol oral solution.

5.3 Interaction with Disulfiram and Metronidazole

Dronabinol oral solution contains 50% (w/w) dehydrated alcohol and 5.5% (w/w) propylene glycol. Use of dronabinol oral solution may cause a disulfiram-like reaction, characterized by abdominal cramps, nausea, vomiting, headaches, and flushing, in patients receiving disulfiram or other drugs that produce this reaction (e.g., metronidazole). Discontinue products containing disulfiram or metronidazole at least 14 days before starting treatment with dronabinol oral solution and do not administer these products within 7 days of completing treatment with dronabinol oral solution [see Contraindications (4), Drug Interactions (7.3)].

When administered concomitantly with propylene glycol, ethanol competitively inhibits the metabolism of propylene glycol, which may lead to elevated concentrations of propylene glycol. However, the contribution of propylene glycol, if any, to the interaction between disulfiram and dronabinol oral solution is unknown.

5.4 Seizures

Seizures and seizure-like activity have been reported in patients receiving dronabinol.

Weigh this potential risk against the benefits before prescribing dronabinol oral solution to patients with a history of seizures, including those receiving anti-epileptic medication or with other factors that can lower the seizure threshold. Monitor patients with a history of seizure disorders for worsened seizure control during dronabinol oral solution therapy.

If a seizure occurs, advise patients to discontinue dronabinol oral solution and contact a healthcare provider immediately.

5.5 Multiple Substance Abuse

Patients with a history of substance abuse or dependence, including marijuana or alcohol, may be more likely to abuse dronabinol oral solution as well. Dronabinol oral solution contains 50% (w/w) dehydrated alcohol.

Assess each patient’s risk for abuse or misuse prior to prescribing dronabinol oral solution and monitor patients with a history of substance abuse during treatment with dronabinol oral solution for the development of these behaviors or conditions.

5.6 Paradoxical Nausea, Vomiting, or Abdominal Pain

New or worsening nausea, vomiting, or abdominal pain can occur during treatment with synthetic delta-9 tetrahydrocannabinol (delta-9-THC), the active ingredient in dronabinol oral solution. In some cases, these adverse reactions were severe (e.g., dehydration, electrolyte abnormalities) and required dose reduction or drug discontinuation. Symptoms are similar to cannabinoid hyperemesis syndrome (CHS), which is described as cyclical events of abdominal pain, nausea, and vomiting in chronic, long-term users of delta-9-THC products.

Because patients may not recognize these symptoms as abnormal, it is important to specifically ask patients or their caregivers about the development or worsening of nausea, vomiting, or abdominal pain while being treated with dronabinol oral solution. Consider dose reduction or discontinuing dronabinol oral solution if a patient develops worsening nausea, vomiting, or abdominal pain while on treatment.

5.7 Toxicity in Preterm Neonates

Dronabinol oral solution contains the excipients dehydrated alcohol (50%, w/w) and propylene glycol (5.5%, w/w). When administered concomitantly with propylene glycol, ethanol competitively inhibits the metabolism of propylene glycol, which may lead to elevated concentrations of propylene glycol. Preterm neonates may be at increased risk of propylene glycol-associated adverse reactions due to a diminished ability to metabolize propylene glycol, thereby, leading to accumulation.

The safety and effectiveness of dronabinol oral solution have not been established in pediatric patients. Avoid dronabinol oral solution in preterm neonates in the immediate postnatal period because of possible propylene glycol-associated toxicities including: hyperosmolarity, with or without lactic acidosis, renal toxicity, CNS depression (including stupor, coma, and apnea), seizures, hypotonia, cardiac arrhythmias, electrocardiogram (ECG) changes, and hemolysis.

6 ADVERSE REACTIONS

6.1 Clinical Trials Experience

Because clinical trials are conducted under widely varying conditions, adverse reaction rates observed in the clinical trials of a drug cannot be directly compared to rates in the clinical trials of another drug and may not reflect the rates observed in practice.

The following serious adverse reactions are described below and elsewhere in the labeling.

- Neuropsychiatric Adverse Reactions [see Warnings and Precautions (5.1)]
- Hemodynamic Instability [see Warnings and Precautions (5.2)]
- Seizures [see Warnings and Precautions (5.4)]
- Paradoxical Nausea, Vomiting, and Abdominal Pain [see Warnings and Precautions (5.6)]
- Toxicity in Preterm Neonates [see Warnings and Precautions (5.7)]

The safety of dronabinol oral solution has been established based on studies of dronabinol capsules. Studies of AIDS-related weight loss included 157 patients receiving dronabinol capsules and 67 receiving placebo. Studies of nausea and vomiting related to cancer chemotherapy included 317 patients receiving dronabinol capsules and 68 receiving placebo. In the tables below is a summary of the adverse reactions in 474 patients exposed to dronabinol capsules in studies.

Studies of different durations were combined by considering the first occurrence of adverse reactions during the first 28 days.

A cannabinoid dose-related “high” (easy laughing, elation and heightened awareness) has been reported by patients receiving dronabinol capsules in both the antiemetic (24%) and the lower dose appetite stimulant clinical trials (8%). The most frequently reported adverse experiences in patients with AIDS during placebo-controlled clinical trials involved the CNS and were reported by 33% of patients receiving dronabinol capsules. About 25% of patients reported a CNS adverse reaction during the first 2 weeks and about 4% reported such a reaction each week for the next 6 weeks thereafter.

Common Adverse Reactions

The following adverse reactions were reported in clinical trials of dronabinol capsules at an incidence greater than 1%.

System Organ Class | Adverse Reactions
General | Asthenia
Cardiovascular | Palpitations, tachycardia, vasodilation/facial flush
Gastrointestinal | Abdominal pain*, nausea*, vomiting*
Central Nervous System | Dizziness*, euphoria*, paranoid reaction*, somnolence*, thinking abnormal*, amnesia, anxiety/nervousness, ataxia, confusion, depersonalization, hallucination
*Actual Incidence 3% to 10%

Less Common Adverse Reactions

The following adverse reactions were reported in clinical trials of dronabinol capsules at an incidence less than or equal to 1%.

System Organ Class | Adverse Reactions
General | Chills, headache, malaise
Cardiovascular | Hypotension, conjunctival injection [see Clinical Pharmacology (12.2)]
Gastrointestinal | Diarrhea, fecal incontinence, anorexia, hepatic enzyme elevation
Musculoskeletal | Myalgias
Central Nervous System | Depression, nightmares, speech difficulties, tinnitus
Respiratory | Cough, rhinitis, sinusitis
Skin | Flushing, sweating
Sensory | Vision difficulties

6.2 Postmarketing Experience

The following adverse reactions have been identified during post-approval use of another oral formulation of dronabinol. Because these reactions are reported voluntarily from a population of uncertain size, it is not always possible to reliably estimate their frequency or establish a causal relationship to drug exposure.

General disorders and administration site conditions: fatigue.

Hypersensitivity reactions: lip swelling, hives, disseminated rash, oral lesions, skin burning, flushing, throat tightness [see Contraindications (4)].

Injury, poisoning and procedural complications: fall [see Use in Specific Populations (8.5)].

Nervous system disorders: seizures [see Warnings and Precautions (5.4)], disorientation, movement disorder, loss of consciousness.

Psychiatric disorders: delirium, insomnia, panic attack.

Vascular disorders: syncope [see Warnings and Precautions (5.2)].

7 DRUG INTERACTIONS

7.1 Disulfiram and Metronidazole

Dronabinol oral solution contains 50% (w/w) dehydrated alcohol and 5.5% (w/w) propylene glycol, which can produce disulfiram-like reactions when co-administered with disulfiram or other drugs that produce this reaction (e.g., metronidazole). Discontinue products containing disulfiram or metronidazole at least 14 days before starting treatment with dronabinol oral solution and do not administer these products within 7 days of completing treatment with dronabinol oral solution [see Contraindications (4), Warnings and Precautions (5.3)].

When administered concomitantly with propylene glycol, ethanol competitively inhibits the metabolism of propylene glycol, which may lead to elevated concentrations of propylene glycol. However, the contribution of propylene glycol, if any, to the interaction between disulfiram and dronabinol oral solution is unknown.

7.2 Effect of Other Drugs on Dronabinol

Dronabinol is primarily metabolized by CYP2C9 and CYP3A4 enzymes. Inhibitors of these enzymes may increase, while inducers may decrease, the systemic exposure of dronabinol and/or its active metabolite resulting in an increase in dronabinol-related adverse reactions or loss of efficacy of dronabinol oral solution.

Monitor for increased dronabinol-related adverse reactions when dronabinol oral solution is co-administered with inhibitors of CYP2C9 (e.g., amiodarone, fluconazole) and inhibitors of CYP3A4 enzymes (e.g., ketoconazole, itraconazole, clarithromycin, ritonavir, erythromycin, grapefruit juice).

7.3 Highly Protein-Bound Drugs

Dronabinol is highly bound to plasma proteins, and therefore, might displace and increase the free fraction of other concomitantly administered protein-bound drugs. Although this displacement has not been confirmed in vivo, monitor patients for increased adverse reactions to narrow therapeutic index drugs (e.g., warfarin, cyclosporine, amphotericin B) when initiating treatment or increasing the dosage of dronabinol oral solution.

8 USE IN SPECIFIC POPULATIONS

8.1 Pregnancy

Risk Summary

Dronabinol oral solution, a synthetic cannabinoid containing alcohol, may cause fetal harm. Avoid use of dronabinol oral solution in pregnant women. Although there is little published data on the use of synthetic cannabinoids during pregnancy, use of cannabis (e.g., marijuana) and use of alcohol during pregnancy have been associated with adverse fetal/neonatal outcomes (see Clinical Considerations). Cannabinoids have been found in the umbilical cord blood from pregnant women who smoke cannabis. In animal reproduction studies, no teratogenicity was reported in mice administered dronabinol (delta-9-THC) at up to 30 times the MRHD (maximum recommended human doses) and up to 5 times the MRHD for patients with AIDS and cancer, respectively. Similar findings were reported in pregnant rats administered dronabinol at up to 5 to 20 times the MRHD and 3 times the MRHD for patients with AIDS and cancer, respectively. Decreased maternal weight gain and number of viable pups and increased fetal mortality and early resorptions were observed in both species at doses which induced maternal toxicity. In rats, maternal administration of dronabinol from pregnancy (implantation) through weaning was associated with maternal toxicity, including mortality of pups, and adverse developmental and neurodevelopmental effects on the pups at 2 to 20 times the MRHD for patients with AIDS and less than and up to 3.3 times the MRHD for patients with cancer. (see Data).

The estimated background risk of major birth defects and miscarriage for the indicated populations are unknown. All pregnancies have a background risk of birth defect, loss, or other adverse outcomes. In the U.S. general population, the estimated background risk of major birth defects and miscarriage in clinically recognized pregnancies is 2 to 4% and 15 to 20%, respectively.

Clinical Considerations

Fetal/Neonatal Adverse Reactions

Published studies suggest that during pregnancy, the use of cannabis, which includes THC, whether for recreational or medicinal purposes, may increase the risk of adverse fetal/neonatal outcomes including fetal growth restriction, low birth weight, preterm birth, small-for-gestational age, admission to the neonatal intensive care unit, and stillbirth. Therefore, use of cannabis during pregnancy should be avoided.

Dronabinol oral solution contains alcohol. Published studies have demonstrated that alcohol is associated with fetal harm including central nervous system abnormalities, behavioral disorders, and impaired intellectual development. Avoid use of Dronabinol oral solution in pregnant women.

Data

Human Data

Delta-9-THC has been measured in the cord blood of some infants whose mothers reported prenatal use of cannabis, suggesting that dronabinol may cross the placenta to the fetus during pregnancy. The effects of delta-9-THC on the fetus are not known.

Animal Data

The recommended dose ranges for dronabinol oral solution in patients with AIDS and patients with cancer are designed to achieve the same systemic exposure ranges to delta-9-THC as with the recommended dose ranges for dronabinol capsules. Therefore, animal to human dose multiples, as shown below, are based on the MRHDs (maximum recommended human doses) for dronabinol capsules, instead of the MRHDs for dronabinol oral solution, which are 15% lower. This approach for dose comparison between animals and humans is supported by the demonstrated difference in dronabinol bioavailability between dronabinol oral solution and dronabinol capsules.

Reproduction studies with dronabinol have been performed in mice at 15 to 450 mg/m^2, equivalent to 1 to 30 times the MRHD of 15 mg/m^2/day (dronabinol capsules) in patients with AIDS or 0.2 to 5 times the MRHD of 90 mg/m^2/day (dronabinol capsules) in patients with cancer, and in rats at 74 to 295 mg/m^2 (equivalent to 5 to 20 times the MRHD of 15 mg/m^2/day in patients with AIDS or 0.8 to 3 times the MRHD of 90 mg/m^2/day in patients with cancer). These studies have revealed no evidence of teratogenicity due to delta-9-THC. At these dronabinol dosages in mice and rats, delta-9-THC decreased maternal weight gain and number of viable pups and increased fetal mortality and early resorptions. Such effects were dose dependent and less apparent at lower doses that produced less maternal toxicity.

Review of published literature indicates that the endocannabinoid system plays a role in neurodevelopmental processes such as neurogenesis, migration, and synaptogenesis. Exposure of pregnant rats to delta-9-THC (during and after organogenesis) may modulate these processes to result in abnormal patterns of neuronal connectivity and subsequent cognitive impairments in the offspring. Nonclinical toxicity studies in pregnant rats and newborn pups have shown prenatal exposure to delta-9-THC that resulted in impairment of motor function, alteration in synaptic activity, and interference in cortical projection of neuron development in the offspring. Prenatal exposure has shown effects on cognitive function such as learning, short- and long-term memory, attention, decreased ability to remember task, and ability to discriminate between novel and same objects. Overall, prenatal exposure to delta-9-THC has resulted in significant and long-term changes in brain development, cognition, and behavior in rat offspring.

In a pre- and post-natal developmental study, female rats administered dronabinol by oral gavage in a vehicle of medium chain triglycerides at doses of 5, 25 and 50 mg/kg/day (equivalent to 1.7, 10, and 20 times the MRHD for patients with AIDS and 0.33, 1.7, and 3.3 times the MRHD for patients with cancer, respectively, based on body surface area) from gestation day 6 (implantation) through lactation day 20 (weaning). Maternal toxicity caused mortality of pups at and above 10 times the MRHD for patients with AIDS and 1.7 times the MRHD for patients with cancer. At 20 times the MRHD for patients with AIDS and 3.3 times the MRHD for patients with cancer, treatment with dronabinol was associated with an increase in the number of dams with 100% pup mortality on lactation days 1 to 4. At 2 and 10 times the MRHD for patients with AIDS and 0.33 and 1.7 times the MRHD for patients with cancer, dronabinol produced adverse effects on the offspring including delays in developmental landmark parameters (e.g., surface righting reflex, negative geotaxis, and air righting reflex), decreased fertility and pregnancy index, reduced ovary and uterus weights, decreased implantations and viable embryos, and increased post-implantation loss.

Neurological adverse effects such as piloerection, landing foot splay and an increase in the number of rears in open field were observed in offspring at 10 and 20 times the MRHD for patients with AIDS and 0.33 and 1.7 times the MRHD for patients with cancer.

Administration of dronabinol in 50% ethanol (used in the vehicle for Dronabinol Oral Solution), was poorly tolerated in maternal animals. Serious adverse signs of toxicity were observed in the control group (vehicle only) and in dronabinol-containing dose groups at 10 and 20 times the MRHD for patients with AIDS and 1.7 and 3.3 times the MRHD for patients with cancer, resulting in termination of all animals at the 50 mg/kg dose level prior to delivery of litters. These animal findings are difficult to interpret due to effects of alcohol in the vehicle.

8.2 Lactation

Risk Summary

For mothers infected with the Human Immunodeficiency Virus (HIV), the Centers for Disease Control and Prevention recommend that HIV-infected mothers not breastfeed their infants to avoid risking postnatal transmission of HIV. Because of the potential for HIV transmission (in HIV-negative infants) and serious adverse reactions in a breastfed infant, instruct mothers not to breastfeed if they are receiving dronabinol oral solution.

For mothers with nausea and vomiting associated with cancer chemotherapy, there are limited data on the presence of dronabinol in human milk, the effects on the breastfed infant, or the effects on milk production. The reported effects of inhaled cannabis transferred to the breastfeeding infant have been inconsistent and insufficient to establish causality. The developmental and health benefits of breastfeeding should be considered along with the mother’s clinical need for dronabinol oral solution and any potential adverse effects on the breastfed infant from dronabinol oral solution or from the underlying maternal condition.

8.4 Pediatric Use

The safety and effectiveness of dronabinol oral solution have not been established in pediatric patients.

Pediatric patients may be more sensitive to neurological and psychoactive effects of dronabinol oral solution [see Warnings and Precautions (5.1)]. Dronabinol oral solution contains the excipients 50% (w/w) dehydrated alcohol and 5.5% (w/w) propylene glycol. Ethanol competitively inhibits the metabolism of propylene glycol, which may lead to elevated concentrations of propylene glycol. Preterm neonates may be at increased risk of propylene glycol-associated adverse events due to diminished ability to metabolize propylene glycol, thereby, leading to accumulation [see Warnings and Precautions (5.7)].

8.5 Geriatric Use

Clinical studies of dronabinol capsules in AIDS and cancer patients did not include sufficient numbers of subjects aged 65 and over to determine whether they respond differently from younger subjects.

Elderly patients may be more sensitive to the neuropsychiatric and postural hypotensive effects of dronabinol oral solution [see Warnings and Precautions (5.1, 5.2)].

Elderly patients with dementia are at increased risk for falls as a result of their underlying disease state, which may be exacerbated by the CNS effects of somnolence and dizziness associated with dronabinol oral solution [see Warnings and Precautions (5.1)]. These patients should be monitored closely and placed on fall precautions prior to initiating dronabinol oral solution therapy. In antiemetic studies, no difference in efficacy was apparent in patients greater than 55 years of age compared to younger patients.

In general, dose selection for an elderly patient should be cautious, usually starting at the low end of the dosing range, reflecting the greater frequency of falls, decreased hepatic, renal, or cardiac function, increased sensitivity to psychoactive effects, and of concomitant disease or other drug therapy [see Dosage and Administration (2.2, 2.3)].

8.6 Effect of CYP2C9 Polymorphism

Published data suggest that systemic clearance of dronabinol may be reduced and concentrations may be increased in presence of CYP2C9 genetic polymorphism. Monitoring for increased adverse reactions is recommended in patients known to carry genetic variants associated with diminished CYP2C9 function [see Clinical Pharmacology (12.5)] .

9 DRUG ABUSE AND DEPENDENCE

9.1 Controlled Substance

Dronabinol oral solution contains dronabinol oral solution, a Schedule II controlled substance.

9.2 Abuse

Dronabinol oral solution contains dronabinol, the main psychoactive component in marijuana. Ingestion of high doses of dronabinol increases the risk of psychiatric adverse reactions if abused or misused, while continued administration can lead to addiction. Psychiatric adverse reactions may include psychosis, hallucinations, depersonalization, mood alteration, and paranoia.

In vitro studies demonstrate that dronabinol oral solution can be easily and effectively abused without manipulation. Dronabinol oral solution contains 50% (w/w) dehydrated alcohol [see Warning and Precautions (5.5)].

In a randomized, single-dose, double-blind, placebo- and active-controlled crossover pharmacodynamic study of 43 experienced marijuana smokers, “drug liking” responses and safety of dronabinol oral solution were compared with placebo and dronabinol in sesame oil oral capsules. Treatment arms were 10 mg and 30 mg dronabinol capsules, 10 mg and 30 mg dronabinol from dronabinol oral solution, and placebo oral solution and capsules. Greater “drug liking” scores were reported with the 30 mg dose, compared with the 10 mg dose, for both dronabinol oral solution and dronabinol-containing capsules. Overall, the pharmacodynamic results from this study demonstrated no statistically significant differences in various measures of drug liking for the doses taken, though the dronabinol oral solution results were consistently greater than those of dronabinol capsules. Similarly, observed adverse reactions were greater for dronabinol oral solution. The pharmacodynamic and safety effects of dronabinol oral solution following multiple doses have not been evaluated.

Patients should be instructed to keep dronabinol oral solution in a secure place out of reach of others for whom the medication has not been prescribed.

9.3 Dependence

Physical dependence is a state that develops as a result of physiological adaptation in response to repeated drug use. Physical dependence manifests by drug class-specific withdrawal symptoms after abrupt discontinuation or a significant dose reduction of a drug. The appearance of a withdrawal syndrome when administration of the drug is terminated is the only actual evidence of physical dependence. Physical dependence can develop during chronic therapy with dronabinol oral solution and develops after chronic abuse of marijuana.

A withdrawal syndrome was reported after the abrupt discontinuation of dronabinol capsules in subjects receiving dosages of 210 mg per day for 12 to 16 consecutive days. Within 12 hours after discontinuation, subjects manifested symptoms such as irritability, insomnia, and restlessness. By approximately 24 hours post-dronabinol discontinuation, withdrawal symptoms intensified to include “hot flashes”, sweating, rhinorrhea, loose stools, hiccoughs, and anorexia. These withdrawal symptoms gradually dissipated over the next 48 hours.

Electroencephalographic changes consistent with the effects of drug withdrawal (hyperexcitation) were recorded in patients after abrupt dechallenge. Patients also complained of disturbed sleep for several weeks after discontinuing therapy with high dosages of dronabinol.

10 OVERDOSAGE

Dronabinol oral solution contains 50% (w/w) dehydrated alcohol and 5.5% (w/w) propylene glycol. Ingestion of the product over the recommended dose could result in significant toxicity.

Dronabinol

Signs and symptoms of dronabinol overdose include drowsiness, euphoria, heightened sensory awareness, altered time perception, reddened conjunctiva, dry mouth, tachycardia, memory impairment, depersonalization, mood alteration, urinary retention, reduced bowel motility, decreased motor coordination, lethargy, slurred speech, and postural hypotension. Patients may also experience panic reactions if they have a prior history of nervousness or anxiety and seizures may occur in patients with existing seizure disorders.

It is not known if dronabinol can be removed by dialysis in cases of overdose.

Alcohol

Signs and symptoms of alcohol overdose include changes in mood or behavior, impaired judgment or social functioning and one or more physical signs such as slurred speech, unsteadiness, lack of coordination, increased or irregular heart rate, respiratory depression, impaired attention or loss of consciousness.

Propylene Glycol

Signs and symptoms of acute poisoning occur only in rare circumstances where patients ingest large amounts of propylene glycol over several days. These include hypoglycemia, severe metabolic acidosis (caused by the metabolism into lactic acid), and CNS depression including coma and seizures.

Management of Overdosage

If over-exposure of dronabinol oral solution occurs, call your Poison Control Center at 1-800-222-1222 for current information on the management of poisoning or overdosage.

11 DESCRIPTION

Dronabinol is a cannabinoid designated chemically as (6aR,10aR)-6a,7,8,10a-Tetrahydro-6,6,9-trimethyl-3-pentyl-6H-dibenzo[b,d]-pyran-1-ol. Dronabinol has the following empirical and structural formulas:

C 21H 30O 2 (molecular weight=314.46)

Dronabinol is a clear colorless to amber oil. Dronabinol is insoluble in water. It has a pKa of 10.6 and an octanol-water partition coefficient: 6,000:1 at pH 7.

Dronabinol oral solution, 5 mg/mL is a clear, pale yellow to brown solution. Each mL of dronabinol oral solution contains 5 mg of dronabinol as an active ingredient and the following inactive ingredients: 50 % (w/w) dehydrated alcohol, polyethylene glycol 400, propylene glycol, sucralose, methyl paraben, propyl paraben, butylated hydroxyanisole, and water.

12 CLINICAL PHARMACOLOGY

12.1 Mechanism of Action

Dronabinol is an orally active cannabinoid that has complex effects on the CNS, including central sympathomimetic activity. Cannabinoid receptors have been discovered in neural tissues. These receptors may play a role in mediating the effects of dronabinol.

12.2 Pharmacodynamics

Effects on the Cardiovascular System

Dronabinol-induced sympathomimetic activity may result in tachycardia and/or conjunctival injection. Its effects on blood pressure are inconsistent, but subjects have experienced orthostatic hypotension and/or syncope upon abrupt standing [see Warnings and Precautions (5.2)].

Effects on the Central Nervous System

Dronabinol also demonstrates reversible effects on appetite, mood, cognition, memory, and perception. These phenomena appear to be dose-related, increasing in frequency with higher dosages, and subject to great inter-patient variability. After oral administration, dronabinol capsules have an onset of action of approximately 0.5 to 1 hours and peak effect at 2 to 4 hours. Duration of action for psychoactive effects is 4 to 6 hours, but the appetite stimulant effect of dronabinol may continue for 24 hours or longer after administration.

Tachyphylaxis and tolerance develop to some of the cardiovascular and CNS pharmacologic effects of dronabinol with chronic use, suggesting an indirect effect on sympathetic neurons. In a study of the pharmacodynamics of chronic dronabinol exposure, healthy male subjects (N = 12) received 12 times the maximum dose for anorexia associated with weight loss in patients with AIDS of dronabinol capsules in divided doses for 16 days. An initial tachycardia induced by dronabinol was replaced successively by normal sinus rhythm and then bradycardia. A decrease in supine blood pressure, made worse by standing, was also observed initially. These subjects developed tolerance to the cardiovascular and subjective adverse CNS effects of dronabinol within 12 days of treatment initiation.

Tachyphylaxis and tolerance do not appear to develop to the appetite stimulant effect of dronabinol. In clinical studies of dronabinol capsules in AIDS patients, at the recommended dosage, the appetite stimulant effect was sustained for up to five months.

12.3 Pharmacokinetics

Absorption

Dronabinol (delta-9-THC) is almost completely absorbed (90 to 95%) after a single oral dose. Due to the combined effects of first pass hepatic metabolism and high lipid solubility, only 10 to 20% of the administered dose reaches the systemic circulation. Relative bioavailability data from healthy male and female subjects suggest that a dose of 4.2 mg of dronabinol oral solution provides comparable systemic exposure (Cmax and AUC) to a 5 mg dronabinol capsule, under fasted conditions [see Dosage and Administration (2.1)]. The concentrations of both dronabinol and its major active metabolite (11-hydroxy-delta-9-THC) peak at approximately 0.5 to 4 hours after oral dosing with dronabinol oral solution and decline over several days. The mean inter- and intra-subject variability in dronabinol pharmacokinetics (Cmax and AUCinf) was approximately 66% and 47% and 67% and 14%, respectively, following administration of dronabinol oral solution to healthy subjects.

Table 1: Summary of Single-Dose Pharmacokinetic Parameters of Dronabinol After Replicated Oral Administration of Dronabinol (4.2 mg to Healthy Subjects under Fasted Conditions)
Parameter* | Dronabinol
C max (ng/mL) | 1.9 ± 1.3
T max (h) | 1.0 [0.5 to 4.0]
AUC (inf) (ng.h/mL) | 3.8 ± 1.8
t ½ (h) | 5.6 ± 2.7
* Arithmetic mean ± standard deviation except Tmax for which the median [range] is reported

Food Effect

The effect of food on the pharmacokinetics of dronabinol oral solution was studied by concomitant dosing of dronabinol oral solution with a high-fat (59 grams of fat, approximately 50% of total caloric content of the meal), high calorie meal (approximately 950 calories). An appreciable food effect was observed: food resulted in approximately a 2.5-fold increase in total exposure (AUCinf) and approximately a 5 hour delay in median Tmax. Food also decreased Cmax by approximately 20% [see Dosage and Administration (2.2, 2.3)].

Distribution

Dronabinol has an apparent volume of distribution of approximately 10 L/kg, because of its lipid solubility. The plasma protein binding of dronabinol and its metabolites is approximately 97% [see Drug Interactions (7.3)].

Elimination

The pharmacokinetics of dronabinol can be described using a two compartment model with an initial (alpha) half-life of about 5 hours and a terminal (beta) half-life of 25 to 36 hours. Values for clearance average about 0.2 L/kg-hr; but are highly variable due to the complexity of cannabinoid distribution.

Metabolism

Dronabinol undergoes extensive first-pass hepatic metabolism, primarily by hydroxylation, yielding both active and inactive metabolites. The major metabolite (11-hydroxy-delta-9-THC) is pharmacologically active. Published in vitro data indicate that CYP2C9 and CYP3A4 are the primary enzymes in the metabolism of dronabinol. CYP2C9 appears to be the enzyme responsible for the formation of the primary active metabolite [see Clinical Pharmacology (12.5)].

Excretion

Dronabinol and its biotransformation products are excreted in both feces and urine. Biliary excretion is the major route of excretion with about half of a radio-labeled oral dose being recovered from the feces within 72 hours as contrasted with 10 to 15% recovered from urine. Less than 5% of an oral dose is recovered unchanged in the feces.

Due to its re-distribution, dronabinol and its metabolites may be excreted for prolonged periods of time. Following single dose administration, dronabinol metabolites have been detected for more than 5 weeks in the urine and feces.

In a study of dronabinol capsules involving AIDS patients, urinary cannabinoid/creatinine concentration ratios were studied bi-weekly over a six week period. The urinary cannabinoid/creatinine ratio was closely correlated with dose. No increase in the cannabinoid/creatinine ratio was observed after the first two weeks of treatment, indicating that steady-state cannabinoid levels had been reached. This conclusion is consistent with predictions based on the observed terminal half-life of dronabinol.

Drug Interaction Studies

Formal drug-drug interaction studies have not been conducted with dronabinol.

The enzyme inhibition and induction potential of dronabinol and its active metabolite are not completely understood.

Published data showed an increase in the elimination half-life of pentobarbital by 4 hours when concomitantly dosed with dronabinol [see Warnings and Precautions (5.1)].

12.5 Pharmacogenomics

Published data indicate a 2- to 3-fold higher dronabinol exposure in individuals carrying genetic variants associated with diminished CYP2C9 function.

13 NONCLINICAL TOXICOLOGY

13.1 Carcinogenesis, Mutagenesis, Impairment of Fertility

The recommended dose ranges for dronabinol oral solution in AIDS and cancer patients are designed to achieve the same systemic exposure ranges as with the recommended dose ranges for dronabinol capsules.

Therefore, the animal to human dose multiples for carcinogenicity studies, as shown below, are based on the MRHD (maximum recommended human dose) for dronabinol capsules in AIDS patients, instead of the MRHD for dronabinol oral solution which is 15% lower. This approach for dose comparison between animals and humans is supported by the demonstrated difference in dronabinol bioavailability between dronabinol oral solution and dronabinol capsules. The animal to human dose multiples for the fertility study in rats, as shown below, are based on the MRHD for dronabinol capsules in AIDS or cancer patients.

In 2-year carcinogenicity studies, there was no evidence of carcinogenicity in rats at doses up to 50 mg/kg/day dronabinol (approximately 20 times the MRHD for dronabinol capsules in AIDS patients on a body surface area basis) or in mice at doses up to 500 mg/kg/day (approximately 100 times the MRHD for dronabinol capsules in AIDS patients on a body surface area basis).

Dronabinol was not genotoxic in the Ames tests, the in vitro chromosomal aberration test in Chinese hamster ovary cells, and the in vivo mouse micronucleus test. However, dronabinol produced a weak positive response in a sister chromatid exchange test in Chinese hamster ovary cells.

In a long-term study (77 days) in rats, oral administration of dronabinol at doses of 30 to 150 mg/m^2, equivalent to 2 to 10 times the MRHD of 15 mg/m^2/day (dronabinol capsules) in AIDS patients or 0.3 to 1.5 times the MRHD of 90 mg/m^2/day (dronabinol capsules) in cancer patients, reduced ventral prostate, seminal vesicle and epididymal weights and caused a decrease in seminal fluid volume. Decreases in spermatogenesis, number of developing germ cells, and number of Leydig cells in the testis were also observed. However, sperm count, mating success and testosterone levels were not affected. The significance of these animal findings in humans is not known.

14 CLINICAL STUDIES

The effectiveness of dronabinol oral solution has been established based on studies of dronabinol capsules for the treatment of anorexia associated with weight loss in patients with AIDS and nausea and vomiting associated with cancer chemotherapy in patients who have failed to respond adequately to conventional antiemetic treatments.

16 HOW SUPPLIED/STORAGE AND HANDLING

- Dronabinol oral solution (dronabinol) oral solution, 5 mg/mL is a clear, pale yellow to brown solution. Dronabinol oral solution is supplied in a multi-dose, clear, amber-colored 30 mL glass bottle. It is closed with a 20 mm child-resistant, white polypropylene screw cap with a Teflon coated liner. The bottle is wrapped with a polyvinyl chloride body band to provide tamper evidence and packaged in a carton with an oral syringe, and a push-in bottle adapter.
  NDC 85776-202-30 (30 mL multi-dose bottle, an oral syringe and a push-in bottle adapter)
- Store in a refrigerator between 2°C and 8°C (36°F and 46°F); excursions permitted up to 25°C (77°F). The opened bottle can be stored at 25°C (77°F). Discard unused portion 42 days after first opening [see USP Controlled Room Temperature].
- Keep Dronabinol oral solution and the oral syringe in the supplied carton.

17 PATIENT COUNSELING INFORMATION

Advise the patient to read the FDA-approved patient labeling (Patient Information and Instructions for Use).

Accidental Ingestion

Inform patients that accidental ingestion of dronabinol oral solution, which contains 50% (w/w) dehydrated alcohol and 5.5% (w/w) propylene glycol, may result in toxicity [see Overdosage (10)]. Instruct patients to seek immediate medical attention in case of accidental ingestion. Also, instruct patients to store dronabinol oral solution securely.

Administration Instructions

- Counsel patients on proper dosing and administration techniques. Advise patients to read the Instructions for Use.
- Instruct patients to take each dronabinol oral solution dose with a full glass of water (6 to 8 ounces).

Neuropsychiatric Adverse Reactions [see Warnings and Precautions (5.1)]

- Advise patients that psychiatric adverse reactions may occur, especially in patients with a past psychiatric history or in those receiving other drugs also associated with psychiatric effects, and to report to their healthcare provider any new or worsening psychiatric symptoms.
- Advise patients, especially elderly patients, that cognitive impairment or an altered mental state may also occur during treatment with dronabinol oral solution and to report to their healthcare provider if they develop signs or symptoms of cognitive impairment.
- Inform patients not to operate motor vehicles or other dangerous machinery until they are reasonably certain that dronabinol oral solution does not affect them adversely.

Hemodynamic Instability

Advise patients, especially those with cardiac disorders, to report to their healthcare provider if they experience any signs or symptoms of hemodynamic instability, including hypotension, hypertension, syncope or tachycardia, especially after initiating or increasing the dosage of dronabinol oral solution [see Warnings and Precautions (5.2)].

Interaction with Disulfiram and Metronidazole

Inform patients that taking dronabinol oral solution with products containing disulfiram or metronidazole may cause a disulfiram-like reaction due to the alcohol content of dronabinol oral solution. Advise patients not to take products containing disulfiram or metronidazole during treatment with dronabinol oral solution and for up to 7 days of completing treatment with dronabinol oral solution [see Warnings and Precautions (5.3)].

Seizures

Advise patients to discontinue dronabinol oral solution and contact a healthcare provider immediately if they experience a seizure [see Warnings and Precautions (5.4)].

Multiple Substance Abuse

Inform patients with a history of substance abuse or dependence, including marijuana or alcohol, that they may be more likely to abuse dronabinol oral solution. Advise patients to report to their healthcare provider if they develop abuse behaviors or conditions [see Warnings and Precautions (5.5)].

Paradoxical Nausea, Vomiting, or Abdominal Pain

Advise patients to report worsening nausea, vomiting, or abdominal pain to their healthcare provider [see Warnings and Precautions (5.6)].

Pregnancy

Advise a pregnant woman of the potential risk to a fetus and to avoid use of dronabinol oral solution during pregnancy. [see Use in Specific Populations (8.1)].

Lactation

Advise HIV infected women with anorexia associated with weight loss, not to breastfeed because HIV can be passed to the baby through the breast milk [see Use in Specific Populations (8.2)].

Manufactured for:
Wellhouse Pharma, LLC
Round Rock, TX 78665
01/2026

PATIENT INFORMATION
dronabinol oral solution, CII

What is the most important information I should know about dronabinol oral solution?

Dronabinol oral solution can cause serious side effects, including:

- Worsening mental (psychiatric) symptoms. Psychiatric symptoms can worsen in people who have mania, depression, or schizophrenia and who take dronabinol oral solution. Dronabinol oral solution taken with medicines that cause psychiatric symptoms can worsen psychiatric symptoms. Elderly people who take dronabinol oral solution may have a greater risk of having psychiatric symptoms. Tell your doctor if you have new or worsening mood symptoms, including symptoms of mania, depression, or schizophrenia.
- Problems thinking clearly. Tell your doctor if you have trouble remembering things, concentrating, have increased sleepiness, or confusion. Elderly people may have a greater risk of having problems thinking clearly.
- Changes in your blood pressure. Dronabinol oral solution may increase or decrease your blood pressure, especially when you start taking dronabinol oral solution or when your dose is changed. Tell your doctor if you have signs or symptoms of changes in your blood pressure including: headaches, vision problems, dizziness, feeling lightheaded, fainting, or a fast heartbeat. Elderly people, especially those with dementia, and people with heart problems may have an increased risk of changes in blood pressure and an increased risk of falls.
- Interactions with disulfiram or metronidazole. Dronabinol oral solution contains alcohol, which can cause you to have a reaction to medicines that contain disulfiram or metronidazole. You should not use any medicine that contains disulfiram (Antabuse) or metronidazole (Pylera, Flagyl, Flagyl ER, Nuvessa, Vandazole) if you take dronabinol oral solution. You should not use a medicine that contains disulfiram or metronidazole for at least 14 days before you start taking dronabinol oral solution and within 7 days after your last dose of dronabinol oral solution .Tell your doctor if you have signs or symptoms of a reaction to disulfiram or metronidazole including: stomach-area (abdominal) cramping, nausea, vomiting, headache, and flushing.

What is dronabinol oral solution ?

- Dronabinol oral solution is a prescription medicine used in adults to treat:
  - loss of appetite (anorexia) in people with AIDS (Acquired Immune Deficiency Syndrome) who have lost weight.
  - nausea and vomiting caused by anti-cancer medicine (chemotherapy) in people whose nausea and vomiting have not improved with usual anti-nausea medicines.

Dronabinol oral solution is a controlled substance (CII) because it contains dronabinol which can be a target for people who abuse prescription medicines or street drugs. Keep your dronabinol oral solution in a safe place to protect it from theft. Never give your dronabinol oral solution to anyone else because it may cause death or harm them. Selling or giving away this medicine is against the law.

It is not known if dronabinol oral solution is safe and effective in children.

Do not take dronabinol oral solution if you:

- had an allergic reaction to dronabinol. Signs and symptoms of an allergic reaction to dronabinol include: swelling of the lips, hives, a rash over your whole body, mouth sores, skin burning, flushing, and throat tightness.
- had an allergic reaction to alcohol.
- are using a medicine that contains disulfiram (Antabuse) or metronidazole (Pylera, Flagyl, Flagyl ER, Nuvessa, Vandazole) or have taken or received a medicine that contains disulfiram or metronidazole in the last 14 days.

Before taking dronabinol oral solution, tell your doctor about all of your medical conditions, including if you:

- have or had heart problems.
- have or had problems with drug abuse or dependence.
- have or had problems with alcohol abuse or dependence.
- have or had mental health problems including mania, depression or schizophrenia.
- have had a seizure or have a medical condition that may increase your risk of having a seizure.
- are pregnant or plan to become pregnant. Dronabinol oral solution may harm your unborn baby. Avoid the use of dronabinol oral solution if you are pregnant.
- are breastfeeding or plan to breastfeed. The Centers for Disease Control and Prevention recommends that mothers with HIV not breastfeed because they can pass the HIV through their breast milk to the baby. It is not known if dronabinol oral solution passes into your breast milk. Talk to your doctor about the best way to feed your baby if you take dronabinol oral solution.

Tell your doctor about all the medicines you take or have taken in the last 14 days, including prescription and over-the-counter medicines, vitamins, and herbal supplements. Dronabinol oral solution and certain other medicines can affect each other, causing serious side effects.

How should I take dronabinol oral solution?

- See the “Instructions for Use” at the end of the Patient Information for detailed instructions about the right way to take dronabinol oral solution by mouth or through a feeding tube, including the types and sizes of feeding tubes that can be used.
- Always use the oral syringe that comes with your dronabinol oral solution to measure your prescribed dose. Ask your doctor or pharmacist to show you how to measure your prescribed dose.
- Take dronabinol oral solution exactly as your doctor tells you to. Your doctor may change your dose after seeing how it affects you. Do not change your dose unless your doctor tells you to change it.
- If you take dronabinol oral solution by mouth, drink a full glass of water (6 to 8 ounces) right after you take your prescribed dose.
- If you take dronabinol oral solution through a feeding tube, flush the feeding tube with 1 ounce (30 mL) of water using a catheter-tip syringe right after you take your prescribed dose.
- If you are an adult with AIDS with loss of appetite and weight loss:
  - Dronabinol oral solution is usually taken 2 times each day, 1 hour before lunch and 1 hour before dinner. If you are elderly, or unable to tolerate this dose of dronabinol oral solution, your doctor may prescribe dronabinol oral solution to be taken 1 time each day, 1 hour before dinner or bedtime.
- If you are an adult with nausea and vomiting caused by anti-cancer medicine:
  - Dronabinol oral solution is usually taken 1 to 3 hours before your chemotherapy treatment and then every 2 to 4 hours after chemotherapy for up to 4 to 6 doses each day. If you are elderly, your doctor may prescribe dronabinol oral solution to be taken 1 to 3 hours before your chemotherapy, 1 time each day.
  - Take your first dose of dronabinol oral solution on an empty stomach at least 30 minutes before eating. After your first dose of dronabinol oral solution, you can take dronabinol oral solution with or without food.
  - After your doctor has decided the dose of dronabinol oral solution that is right for you, take dronabinol oral solution exactly at the same time before or after meals during future chemotherapy treatment.
- If you take too much dronabinol oral solution, call your Poison Control Center at 1-800-222-1222 right away or go to the nearest emergency room.

What should I avoid while taking dronabinol oral solution?

- Do not drive, operate machinery, or do other dangerous activities until you know how dronabinol oral solution affects you. Dronabinol oral solution taken with medicines that cause dizziness, confusion, and sleepiness may make these symptoms worse.

What are the possible side effects of dronabinol oral solution?

Dronabinol oral solution may cause serious side effects, including:

- See “What is the most important information I should know about dronabinol oral solution?”
- Seizures. Dronabinol oral solution may increase your risk of seizures. Stop taking dronabinol oral solution and call your doctor and get medical care right away if you have a seizure during treatment with dronabinol oral solution.
- Drug and alcohol abuse. You may have an increased risk of abusing dronabinol oral solution if you have a history of drug or alcohol abuse or dependence, including marijuana. Tell your doctor if you develop abuse behaviors such as increased irritability, nervousness, restlessness or want more or higher doses of dronabinol oral solution during your treatment.
- Nausea, vomiting, or stomach-area (abdominal) pain. Tell your doctor if you have nausea, vomiting, or abdominal pain or if your nausea, vomiting, or abdominal pain gets worse during treatment with dronabinol oral solution.

The most common side effects of dronabinol oral solution include:

- stomach-area (abdominal) pain
- dizziness
- feeling extremely happy (euphoria)
- nausea
- overly suspicious or feeling people want to harm you (paranoid reaction)

- sleepiness
- abnormal thoughts
- vomiting

These are not all the possible side effects of dronabinol oral solution. Tell your doctor if you have any side effect that bothers you or does not go away. Call your doctor for medical advice about side effects. You may report side effects to FDA at 1-800-FDA-1088.

General information about the safe and effective use of dronabinol oral solution.

Medicines are sometimes prescribed for purposes other than those listed in a Patient Information leaflet. Do not use dronabinol oral solution for a condition for which it was not prescribed. Do not give dronabinol oral solution to other people, even if they have the same symptoms that you have. It may harm them. You can ask your doctor or pharmacist for information about dronabinoloral solution that is written for health professionals.

What are the ingredients in dronabinol oral solution?

Active ingredient: dronabinol

Inactive ingredients: dehydrated alcohol, polyethylene glycol 400, propylene glycol, sucralose, methyl paraben, propyl paraben, butylated hydroxyanisole, and water.

Issued: 01/2026

INSTRUCTIONS FOR USE
Dronabinol
Oral Solution, CII

Read this Instructions for Use before you start taking dronabinol oral solution and each time you get a refill. There may be new information. This information does not take the place of talking to your doctor about your medical condition or your treatment.

Important information about measuring dronabinol oral solution:

- Always use the oral syringe that comes with your dronabinol oral solution to measure your prescribed dose. Ask your doctor or pharmacist to show you how to measure your prescribed dose.

Important information about giving dronabinol oral solution through a feeding tube:

- Give dronabinol oral solution through feeding tubes that are made with silicone and that are size 14 French or larger. Do not give dronabinol oral solution through feeding tubes that are not made with silicone or that are smaller than size 14 French.
- Do not use feeding tubes made with polyurethane.
- Dronabinol oral solution can be given through a naso-gastric tube (NG tube), gatrostomy tube (G-tube), percutaneous endoscopic gastrostomy tube (PEG-tube), and gastro-jejunostomy tube (GJ-tube).

- Each dronabinol oral solution carton contains (See Figure A):
  - 1 bottle of dronabinol oral solution
  - 1 oral syringe
  - 1 adapter (You will need to insert the adapter into the bottle before using the bottle for the first time.)
  The contents in the dronabinol carton are wrapped in plastic. Do not use the contents if they are not wrapped in plastic when you receive them.

Call Wellhouse Pharma at 1-844-558-8289 if:

- you do not receive an oral syringe or adapter with your dronabinol oral solution
- you lose the oral syringe that comes with dronabinol oral solution
- the contents in the dronabinol oral solution carton are not wrapped in plastic when you receive them.

How to prepare a bottle of Dronabinol oral solution before using for the first time:
Step 1: Remove the plastic wrap from the bottle and throw it away.
Step 2: Open the bottle by pushing down firmly on the child-resistant cap and turning it counter-clockwise (See Figure B). Do not throw away the child-resistant cap.

Step 3: Remove the adapter from the plastic wrap. You may need to use a pair of scissors.
Step 4: Place the open bottle upright on a flat surface. Firmly push down on the adapter until the ribbed end of the adapter fits into the neck of the bottle as far as it will go and is firmly in place (See Figure C). The top edge of the adapter should be in full contact with the top rim of the bottle. Do not remove the adapter from the bottle after it is inserted.
Step 5: Follow the instructions in “How to prepare a dose of dronabinol oral solution after the adapter is inserted.”

How to prepare a dose of dronabinol oral solution after the adapter is inserted:

Step 1: Open the bottle by pushing down firmly on the child-resistant cap and turning it counter-clockwise (See Figure D). Do not throw away the child-resistant cap.

Step 2: If you are using the oral syringe for the first time, remove the oral syringe from the plastic wrap. You may need to use a pair of scissors.
Step 3: Hold the oral syringe in one hand. With your other hand, fully push down (depress) the plunger (See Figure E).

Step 4: Keeping the bottle in an upright position, insert the syringe tip firmly into the adapter (See Figure F).

Step 5: Carefully turn the bottle upside down with the syringe tip firmly inserted into the adapter (See Figure G).

Step 6: Slowly pull back on the plunger until the measuring ring is at the line marking for the dose prescribed by your doctor. The measuring ring is the widest part of the plunger at the bottom of the tip of plunger. (See Figures H(a) and H(b)). Figure H(a) shows a dose of 0.4 mL as an example.
If you see air bubbles in the oral syringe, fully push in the plunger so that the oral solution flows back into the bottle. Then, withdraw your prescribed dose of oral solution.
If your prescribed dose is more than 1 mL, you will need to draw up two or more doses.
For example, if your dose is 1.2 mL, you will need to draw up a 1 mL dose followed by a 0.2 mL dose.

Step 7: Leave the oral syringe in the adapter and turn the bottle to an upright position. Place the bottle onto a flat surface. Remove the oral syringe from the bottle adapter by gently pulling straight up on the oral syringe (See Figure I).

Step 8: Check that the correct dose of Dronabinol oral solution was drawn up into the oral syringe.

If the dose is not correct, insert the syringe tip firmly into the bottle adapter. Fully push in the plunger so that the oral solution flows back into the bottle (See Figure J).
Repeat Steps 5-8.

If you are taking your dose of dronabinol oral solution by mouth, follow the instructions in “How to take a dose of dronabinol oral solution by mouth.”

If you are taking your dose of dronabinol oral solution through a feeding tube, follow the instructions in “How to take a dose of dronabinol oral solution through a feeding tube.”

How to take a dose of dronabinol oral solution by mouth:

Step 1: Open your mouth. Place the oral syringe tip in the back of your mouth on top of your tongue. Tilt your head back slightly and close your lips around the barrel of the oral syringe. Slowly push down the plunger until the oral syringe is empty (See Figure K).
Swallow the oral solution.

If your prescribed dose is more than 1 mL, repeat Steps 4-8 in “How to prepare a dose of dronabinol oral solution after the adapter is inserted” to draw up the remaining dose until the prescribed dose is given. For example, if your prescribed dose is 1.6 mL, take a 1 mL dose first, then an additional dose of 0.6 mL.

Take your dronabinol oral solution right away after it is drawn up into the oral syringe.

Step 2: Drink a full glass of water (6 to 8 ounces) right after you take your prescribed dose of dronabinol oral solution (See Figure L).

Step 3: Leave the adapter in the bottle. Put the child-resistant cap back on the bottle (See Figure M).

Step 4: Remove the plunger from the oral syringe barrel. Rinse the oral syringe barrel and plunger with warm water after each use and let them air dry. When the oral syringe barrel and plunger are dry, put the plunger back into the oral syringe barrel for the next use. Keep Dronabinol oral solution and the oral syringe in the carton that it comes in. Do not throw away the oral syringe.

How to take a dose of dronabinol oral solution through a feeding tube:

See “Important information about giving dronabinol oral solution through a feeding tube.”

Step 1: Place the oral syringe into the feeding tube. Slowly push down the plunger until the oral syringe is empty (See Figure N).

If your prescribed dose is more than 1 mL, repeat Steps 4-8 in “How to prepare a dose of dronabinol oral solution after the adapter is inserted” to draw up the remaining dose until the prescribed dose is given. For example, if your prescribed dose is 1.6 mL, take a 1 mL dose first, then an additional dose of 0.6 mL.

Take your dronabinol oral solution right away after it is drawn up into the oral syringe.

Step 2: Using a catheter-tip syringe, flush the feeding tube with 1 ounce (30 mL) of water (See Figure O).

Step 3: Leave the adapter in the bottle. Put the child-resistant cap back on the bottle (See Figure P).

Step 4: Remove the plunger from the oral syringe barrel. Rinse the oral syringe barrel and plunger with warm water after each use and let them air dry. When the oral syringe barrel and plunger are dry, put the plunger back into the oral syringe barrel for the next use. Keep Dronabinol oral solution and the oral syringe in the carton that it comes in.

Do not throw away the oral syringe.

How should I store dronabinol oral solution?

- Store dronabinol oral solution in the refrigerator between 36°F and 46°F (2°C and 8°C).
- After the bottle is opened, dronabinol oral solution can be stored at room temperature, between 68°F and 77°F (20°C and 25°C), for up to 42 days.
- Do not use dronabinol oral solution that has been stored in the refrigerator or at room temperature 42 days after opening the bottle. Write the date that you open the bottle of dronabinol oral solution on the bottle and carton it comes in. See “How should I dispose of unused dronabinol oral solution?”

Keep dronabinol and all medicines out of the reach of children.

How should I dispose of unused dronabinol oral solution?

- Dispose of unused dronabinol oral solution as soon as you no longer need it or 42 days after opening the bottle.

Talk to your doctor or pharmacist if you have questions about how to use dronabinol oral solution.
For more information, call 1-844-558-8289.
This Patient Information and Instructions for Use have been approved by the U.S. Food and Drug Administration.

Wellhouse Pharmaceuticals LLC
Round Rock, TX 78665

Revised: January 2026

PACKAGE LABEL

PRINCIPAL DISPLAY PANEL - NDC: 85776-202-30 - 30 mL Carton Label

NDC 85776-202-30
Dronabinol CII
Oral Solution
5 mg/mL
Dispense
in original container
with oral syringe
for administration
Pharmacist: Dispense with Patient Information
Leaflet and Instructions for Use provided
separately
For oral administration only
Rx only
30 mL
Before use: Must be refrigerated,
store between 2° and 8° C (36°
and 46°F). Once opened, the
bottle can be stored at room
temperature.
Date of first opening
______/______/______
Discard unused portion 42 days
after opening.
Container includes:

- 30mL light resistant bottle
  containing 150mg dronabinol
  (50mg/mL)
- Oral syringe
- Adapter

Pharmacists: Provide patients with
dosing instructions in milliliters (mL)
and round dose to nearest 0.1 mL
increment.
PROTECT FROM LIGHT.
DO NOT USE IF TAMPER EVIDENT SEAL
IS BROKEN OR MISSING.
Dosage: See accompanying package insert for
full prescribing information. Each milliliter of
dronabinol oral solution contains 5mg
dronabinol, 50% w/w dehydrated alcohol,
propylene glycol, polyethylene glycol 400,
sucralose, methyl paraben, propyl paraben,
butylated hydroxyanisole and water. Protect
from light by keeping bottle and carton until
consumed.
KEEP THIS AND ALL MEDICATIONS OUT
OF THE REACH OF CHILDREN
Manufactured for: Wellhouse Pharma LLC
Round Rock, TX
GTIN 00199874020396
PN.01034 REV. 00 01/26
SN: XXXXXXXXXXXXXX
LOT: XXXXXXX
EXP: MM/YEAR

PACKAGE LABEL

PRINCIPAL DISPLAY PANEL - NDC: 85776-202-30 - 30 mL Bottle Label

NDC 85776-202-30
Dronabinol CII
Oral Solution
5 mg/mL
Dispense in original container with
oral syringe for administration
For oral administration only
Rx only
30 mL
Wellhouse
PROTECT FROM LIGHT. DO NOT USE IF TAMPER EVIDENT
SEAL IS BROKEN OR MISSING.
Dosage: See accompanying package insert for full prescribing
information. Each milliliter of dronabinol oral solution contains 5mg
dronabinol, 50% w/w dehydrated alcohol, propylene glycol,
polyethylene glycol 400,sucralose, methyl paraben, propyl
paraben, butylated hydroxyanisole and water.
Before use: Must be refrigerated, store between 2° and 8° C
(36°and 46°F).
Once opened, the bottle can be stored at room temperature.
Date of first opening
______/______/______
Discard unused portion 42 days after opening.
KEEP OUT OF THE REACH OF CHILDREN
GTIN 00199874020396 PN.01033 REV. 00 01/26
Manufactured for: Wellhouse Pharma LLC
Round Rock, TX
LOT: XXXXXXX
EXP: MM/YEAR